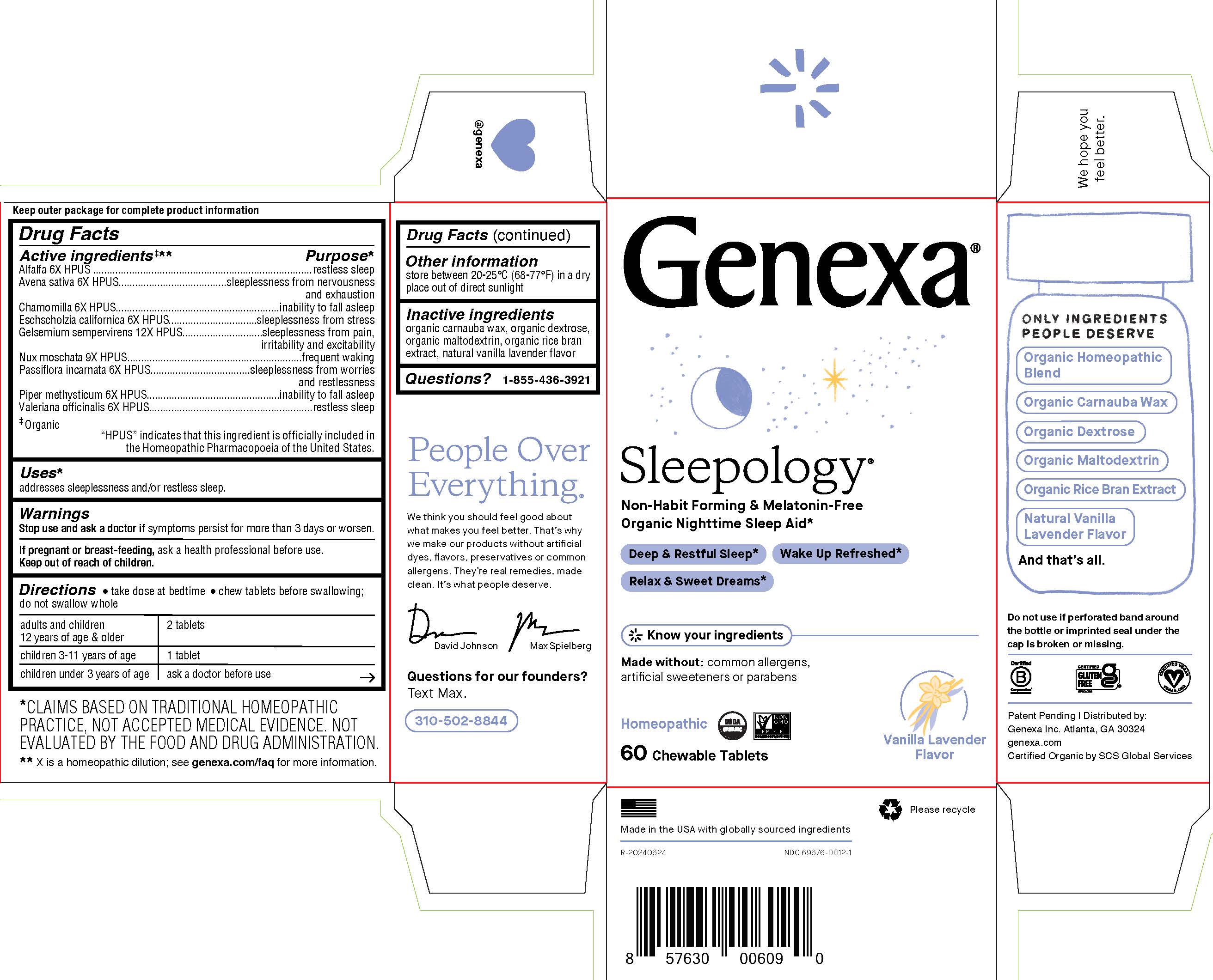 DRUG LABEL: Sleepology
NDC: 69676-0012 | Form: TABLET, CHEWABLE
Manufacturer: Genexa Inc.
Category: homeopathic | Type: HUMAN OTC DRUG LABEL
Date: 20250402

ACTIVE INGREDIENTS: AVENA SATIVA FLOWERING TOP 6 [hp_X]/1 1; ALFALFA 6 [hp_X]/1 1; ESCHSCHOLZIA CALIFORNICA 6 [hp_X]/1 1; PASSIFLORA INCARNATA FLOWERING TOP 6 [hp_X]/1 1; NUTMEG 9 [hp_X]/1 1; VALERIAN 6 [hp_X]/1 1; PIPER METHYSTICUM ROOT 6 [hp_X]/1 1; GELSEMIUM SEMPERVIRENS ROOT 12 [hp_X]/1 1; MATRICARIA CHAMOMILLA WHOLE 6 [hp_X]/1 1
INACTIVE INGREDIENTS: DEXTROSE; CARNAUBA WAX; MALTODEXTRIN; RICE BRAN

SLEEPOLOGY

Drug Facts

Active ingredients‡**

Alfalfa 6X HPUS

Avena sativa 6X HPUS

Chamomilla 6X HPUS

Eschscholzia californica 6X HPUS

Gelsemium sempervirens 12X HPUS

Nux moschata 9X HPUS

Passiflora incarnata 6X HPUS

Piper methysticum 6X HPUS

Valeriana officinalis 6X HPUS

‡ Organic

"HPUS" indicates that this ingredient is officially included in the Homoeopathic Pharmacopoeia of the United States.

Purpose*

restless sleep

sleeplessness from nervousness and exhaustion

inability to fall asleep

sleeplessness from stress

sleeplessness from pain, irritability and excitability

frequent waking

sleeplessness from worries and restlessness

inability to fall asleep

restless sleep

Uses*

addresses sleeplessness and/or restless sleep.

Warnings

Stop use and ask a doctorif symptoms persist for more than 3 days or worsen.

PREGNANCY OR BREAST FEEDING

If pregnant or breast-feeding, ask a health professional before use.

Keep out of reach of children.

Directions

- take dose at bedtime
- chew tablets before swallowing; do not swallow whole

adults and children 12 years of age and older | 2 tablets
children 3-11 years of age | 1 tablet
children under 3 years of age | ask a doctor before use

Other information

store between 20-25°C (68-77°F) in a dry place out of direct sunlight

Inactive ingredients

organic carnuaba wax, organic dextrose, organic maltodextrin, organic rice bran extract, natural vanilla lavender flavor

Questions?

1-855-436-3921

* CLAIMS BASED ON TRADITIONAL HOMEOPATHIC PRACTICE. NOT ACCEPTED MEDICAL EVIDENCE. NOT EVALUATED BY THE FOOD AND DRUG ADMINISTRATION.
** X is a homeopathic dilution; see genexa.com/faq for more information.

Do not use if perforated band around the bottle or imprinted seal under the cap is broken or missing.

Patent Pending | Distributed by:

Genexa Inc. Atlanta, GA 30324
genexa.com
Certified Organic by SCS Global Services

Made in the USA with globally sourced ingredients

NDC 69676-0012-1

Directions

- take dose at bedtime
- chew tablets before swallowing; do not swallow whole

adults and children 12 years of age and older | 2 tablets
children 3-11 years of age | 1 tablet
children under 3 years of age | ask a doctor before use

PACKAGE LABEL

Genexa®

Sleepology

Non-Habit Forming & Melatonin-Free

Organic Nighttime Sleep Aid*

Deep and Restful Sleep*

Wake Up Refreshed*

Relax and Sweet Dreams*

Know your ingredients

Made without: common allergens, artificial sweeteners or parabens

Homeopathic

Vanilla Lavender Flavor

60 Chewable Tablets